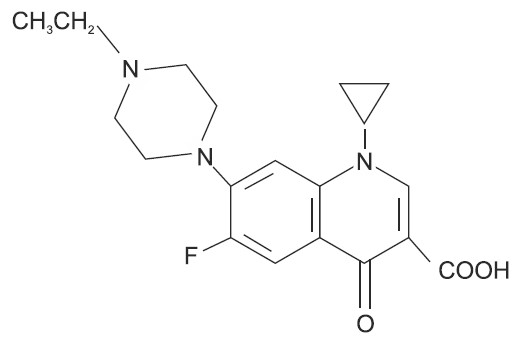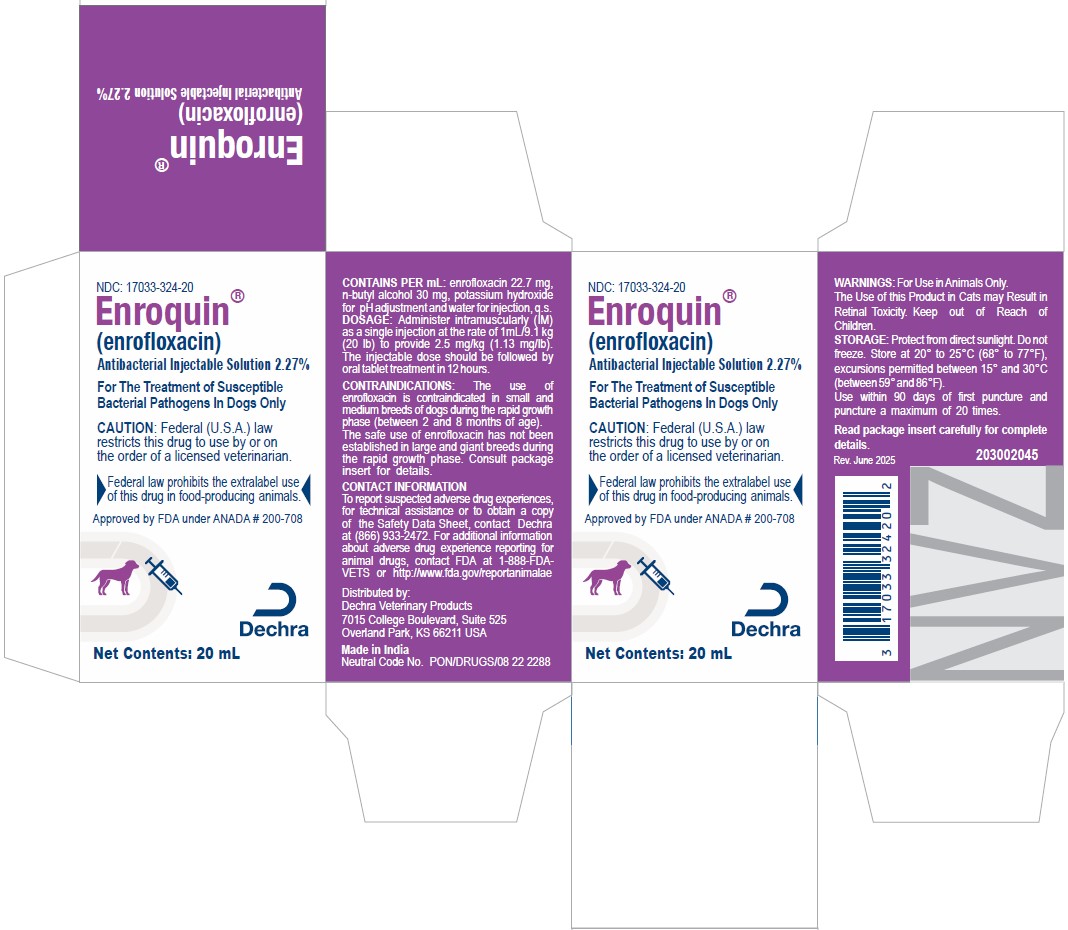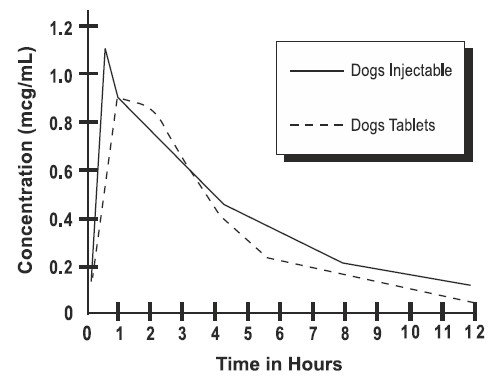 DRUG LABEL: Enroquin
NDC: 17033-324 | Form: INJECTION, SOLUTION
Manufacturer: Dechra Veterinary Products, LLC
Category: animal | Type: PRESCRIPTION ANIMAL DRUG LABEL
Date: 20260226

ACTIVE INGREDIENTS: Enrofloxacin 22.7 mg/1 mL

Enroquin®
(enrofloxacin)

SAFE HANDLING WARNING

NDC No. 17033-324-20

Antibacterial Injectable Solution 2.27%
For Dogs Only

VETERINARY INDICATIONS

CAUTION:

Federal (U.S.A.) law restricts this drug to use by or on the order of a licensed veterinarian.

► Federal law prohibits the extralabel use of this drug in food-producing animals. ◄

DESCRIPTION:

Enrofloxacin is a synthetic chemotherapeutic agent from the class of the quinolone carboxylic acid derivatives. It has antibacterial activity against a broad spectrum of Gram negative and Gram positive bacteria (See Tables I and II). Each mL of injectable solution contains: enrofloxacin 22.7 mg, n-butyl alcohol 30 mg, potassium hydroxide for pH adjustment and water for injection, q.s.

CHEMICAL NOMENCLATURE AND STRUCTURAL FORMULA:

1-cyclopropyl-7-(4-ethyl-1-piperazinyl)-6-fluoro-1,4-dihydro-4-oxo-3-quinolinecarboxylic acid.

MECHANISM OF ACTION

ACTIONS:

MICROBIOLOGY

Microbiology: Quinolone carboxylic acid derivatives are classified as DNA gyrase inhibitors. The mechanism of action of these compounds is very complex and not yet fully understood. The site of action is bacterial gyrase, a synthesis promoting enzyme. The effect on Escherichia coli is the inhibition of DNA synthesis through prevention of DNA supercoiling. Among other things, such compounds lead to the cessation of cell respiration and division. They may also interrupt bacterial membrane integrity.^1

Enrofloxacin is bactericidal, with activity against both Gram negative and Gram positive bacteria. The minimum inhibitory concentrations (MICs) were determined for a series of 37 isolates representing 9 genera of bacteria from natural infections in dogs, selected principally because of resistance to one or more of the following antibiotics: ampicillin, cephalothin, colistin, chloramphenicol, erythromycin, gentamicin, kanamycin, penicillin, streptomycin, tetracycline, triple sulfa and sulfa/trimethoprim. The MIC values for enrofloxacin against these isolates are presented in Table I. Most strains of these organisms were found to be susceptible to enrofloxacin in vitro but the clinical significance has not been determined for some of the isolates.

The susceptibility of organisms to enrofloxacin should be determined using enrofloxacin 5 mcg disks. Specimens for susceptibility testing should be collected prior to the initiation of enrofloxacin therapy.

TABLE I-MIC Values for Enrofloxacin Against Canine Pathogens (Diagnostic laboratory isolates, 1984)
Organisms | Isolates | MIC Range (mcg/mL)
Bacteroides spp. | 2 | 2
Bordetella bronchiseptica | 3 | 0.125-0.5
Brucella canis | 2 | 0.125-0.25
Clostridium perfringens | 1 | 0.5
Escherichia coli | 4 | ≤0.016-0.031
Klebsiella spp. | 10 | 0.031-0.5
Proteus mirabilis | 6 | 0.062-0.125
Pseudomonas aeruginosa | 4 | 0.5-8
Staphylococcus spp. | 5 | 0.125

The inhibitory activity on 120 isolates of seven canine urinary pathogens was also investigated and is listed in Table II.

TABLE II - MIC Values for Enrofloxacin Against Canine Urinary Pathogens (Diagnostic laboratory isolates, 1985)
Organisms | Isolates | MIC Range (mcg/mL)
E. coli | 30 | 0.06-2.0
P. mirabilis | 20 | 0.125-2.0
K. pneumoniae | 20 | 0.06-0.5
P. aeruginosa | 10 | 1.0-8.0
Enterobacter spp. | 10 | 0.06-1.0
Staph. (coag. +) | 20 | 0.125-0.5
Strep. (alpha hemol.) | 10 | 0.5-8.0

Distribution in the Body: Enrofloxacin penetrates into all canine tissues and body fluids. Concentrations of drug equal to or greater than the MIC for many pathogens (See Tables I, II and III) are reached in most tissues by two hours after dosing at 2.5 mg/kg and are maintained for 8-12 hours after dosing. Particularly high levels of enrofloxacin are found in urine. A summary of the body fluid/tissue drug levels at 2 to 12 hours after dosing at 2.5 mg/kg is given in Table III.

TABLE III - Body Fluid/Tissue distribution of Enrofloxacin in Dogs
Single Oral Dose = 2.5 mg/kg (1.13 mg/lb)
 | Post-treatment Enrofloxacin Levels Canine (n=2)
Body Fluids (mcg/mL) | 2 Hr. | 8 Hr.
Urine | 43.05 | 55.35
Eye Fluids | 0.53 | 0.66
Whole Blood | 1.01 | 0.36
Plasma | 0.67 | 0.33
Tissues (mcg/g) Hematopoietic System
Liver | 3.02 | 1.36
Spleen | 1.45 | 0.85
Bone Marrow | 2.10 | 1.22
Lymph Node | 1.32 | 0.91
Urogenital System
Kidney | 1.87 | 0.99
Bladder Wall | 1.36 | 0.98
Testes | 1.36 | 1.10
Prostate | 1.36 | 2.20
Uterine Wall | 1.59 | 0.29
Gastrointestinal and Cardiopulmonary Systems
Lung | 1.34 | 0.82
Heart | 1.88 | 0.78
Stomach | 3.24 | 2.16
Small Intestine | 2.10 | 1.11
Other
Fat | 0.52 | 0.40
Skin | 0.66 | 0.48
Muscle | 1.62 | 0.77
Brain | 0.25 | 0.24
Mammary Gland | 0.45 | 0.21
Feces | 1.65 | 9.97

PHARMACOKINETICS

Pharmacokinetics: In dogs, the absorption and elimination characteristics of the oral formulation are linear (plasma concentrations increase proportionally with dose) when enrofloxacin is administered at up to 11.5 mg/kg, twice daily.2 Approximately 80% of the orally administered dose enters the systemic circulation unchanged. The eliminating organs, based on the drug's body clearance time, can readily remove the drug with no indication that the eliminating mechanisms are saturated. The primary route of excretion is via the urine. The absorption and elimination characteristics beyond this point are unknown. Saturable absorption and/or elimination processes may occur at greater doses. When saturation of the absorption process occurs, the plasma concentration of the active moiety will be less than predicted, based on the concept of dose proportionality.

Following an oral dose in dogs of 2.5 mg/kg (1.13 mg/lb), enrofloxacin reached 50% of its maximum serum concentration in 15 minutes and peak serum level was reached in one hour. The elimination half-life in dogs is approximately 2½-3 hours at that dose.

A graph indicating the mean serum levels following a dose of 2.5 mg/kg (1.13 mg/lb) in dogs (oral and intramuscular) is shown in Figure 1.

Figure 1 - Serum Concentrations of Enrofloxacin Following a Single Oral or Intramuscular Dose at 2.5 mg/kg in Dogs.

Breakpoint: Based on pharmacokinetic studies of enrofloxacin in dogs after a single oral administration of 2.5 mg enrofloxacin/kg BW (i.e. half of the lowest-end single daily dose range) and the data listed in Tables I and II, the following breakpoints are recommended for canine isolates.

Zone Diameter (mm) | MIC (μg/mL) | Interpretation
≥21 | ≤0.5 | Susceptible (S)
18 - 20 | 1 | Intermediate (I)
≤17 | ≥2 | Resistant (R)

A report of "Susceptible" indicates that the pathogen is likely to be inhibited by generally achievable plasma levels. A report of "Intermediate" is a technical buffer and isolates falling into this category should be retested. Alternatively the organism may be successfully treated if the infection is in a body site where drug is physiologically concentrated. A report of "resistant" indicates that the achievable drug concentrations are unlikely to be inhibitory and other therapy should be selected.

Standardized procedures require the use of laboratory control organisms for both standardized disk diffusion assays and standardized dilution assays. The 5 µg enrofloxacin disk should give the following zone diameters and enrofloxacin powder should provide the following MIC values for reference strains.

QC strains | MIC (μg/mL) | Zone Diameter (mm)
E. coli ATCC 25922 | 0.008 - 0.03 | 32 - 40
P. aeruginosa ATCC 27853 | 1 - 4 | 15 - 19
S. aureus ATCC 25923 |  | 27 - 31
S. aureus ATCC 29213 | 0.03 - 0.12

INDICATIONS:

Enroquin® (enrofloxacin) Injectable Solution is indicated for the management of diseases in dogs associated with bacteria susceptible to enrofloxacin.

EFFICACY CONFIRMATION:

Clinical efficacy was established in dermal infections (wounds and abscesses) associated with susceptible strains of Escherichia coli, Klebsiella pneumoniae, Proteus mirabilis, and Staphylococcus intermedius; respiratory infections (pneumonia, tonsillitis, rhinitis) associated with susceptible strains of Escherichia coli and Staphylococcus aureus; and urinary cystitis associated with susceptible strains of Escherichia coli, Proteus mirabilis, and Staphylococcus aureus.

CONTRAINDICATIONS:

Enrofloxacin is contraindicated in dogs known to be hypersensitive to quinolones.

Based on the studies discussed under the section on Animal Safety Summary, the use of enrofloxacin is contraindicated in small and medium breeds of dogs during the rapid growth phase (between 2 and 8 months of age). The safe use of enrofloxacin has not been established in large and giant breeds during the rapid growth phase. Large breeds may be in this phase for up to one year of age and the giant breeds for up to 18 months. In clinical field trials utilizing a daily oral dose of 5.0 mg/kg, there were no reports of lameness or joint problems in any breed. However, controlled studies with histological examination of the articular cartilage have not been conducted in the large or giant breeds.

ADVERSE REACTIONS:

No drug-related side effects were reported in 122 clinical cases treated with enrofloxacin injectable solution followed by enrofloxacin tablets at 5.0 mg/kg per day.

CONTACT INFORMATION

To report suspected adverse drug experiences, for technical assistance or to obtain a copy of the Safety Data Sheet, contact Dechra at (866) 933 2472. For additional information about adverse drug experience reporting for animal drugs, contact FDA at 1-888-FDA-VETS or http://www.fda.gov/reportanimalae

ANIMAL SAFETY SUMMARY:

Adult dogs receiving enrofloxacin orally at a daily dosage rate 52 mg/kg for 13 weeks had only isolated incidences of vomition and inappetence. Adult dogs receiving the tablet formulation for 30 consecutive days at a daily treatment of 25 mg/kg did not exhibit significant clinical signs nor were there effects upon the clinical chemistry, hematological or histological parameters. Daily doses of 125 mg/kg for up to 11 days induced vomition, inappetence, depression, difficult locomotion and death while adult dogs receiving 50 mg/kg/day for 14 days had clinical signs of vomition and inappetence.

Adult dogs dosed intramuscularly for three treatments at 12.5 mg/kg followed by 57 oral treatments at 12.5 mg/kg, all at 12 hour intervals, did not exhibit either significant clinical signs or effects upon the clinical chemistry, hematological or histological parameters.

Oral treatment of 15 to 28 week old growing puppies with daily dosage rates of 25 mg/kg has induced abnormal carriage of the carpal joint and weakness in the hindquarters. Significant improvement of clinical signs is observed following drug withdrawal. Microscopic studies have identified lesions of the articular cartilage following 30 day treatments at either 5, 15 or 25 mg/kg in this age group. Clinical signs of difficult ambulation or associated cartilage lesions have not been observed in 29 to 34 week old puppies following daily treatments of 25 mg/kg for 30 consecutive days nor in 2 week old puppies with the same treatment schedule.

Tests indicated no effect on circulating microfilariae or adult heartworms (Dirofilaria immitis) when dogs were treated at a daily dosage rate of 15 mg/kg for 30 days. No effect on cholinesterase values was observed.

No adverse effects were observed on reproductive parameters when male dogs received 10 consecutive daily treatments of 15 mg/kg/day at 3 intervals (90, 45 and 14 days) prior to breeding or when female dogs received 10 consecutive daily treatments of 15 mg/kg/day at 4 intervals; between 30 and 0 days prior to breeding, early pregnancy (between 10th & 30th days), late pregnancy (between 40th & 60th days), and during lactation (the first 28 days).

DRUG INTERACTIONS:

Concomitant therapy with other drugs that are metabolized in the liver may reduce the clearance rates of the quinolone and the other drug.

Enrofloxacin has been administered to dogs at a daily dosage rate of 10 mg/kg concurrently with a wide variety of other health products including anthelmintics (praziquantel, febantel), insecticides (pyrethrins), heartworm preventatives (diethylcarbamazine) and other antibiotics (ampicillin, gentamicin sulfate, penicillin). No incompatibilities with other drugs are known at this time.

WARNINGS:

For use in animals only. The use of this product in cats may result in Retinal Toxicity. Keep out of reach of children. Avoid contact with eyes. In case of contact, immediately flush eyes with copious amounts of water for 15 minutes. In case of dermal contact, wash skin with soap and water. Consult a physician if irritation persists following ocular or dermal exposure. Individuals with a history of hypersensitivity to quinolones should avoid this product. In humans, there is a risk of user photosensitization within a few hours after excessive exposure to quinolones. If excessive accidental exposure occurs, avoid direct sunlight.

For customer service or to obtain product information, including Safety Data Sheet, call (866) 933-2472.

PRECAUTIONS

PRECAUTION:

Quinolone-class drugs should be used with caution in animals with known or suspected Central Nervous System (CNS) disorders. In such animals, quinolones have, in rare instances, been associated with CNS stimulation which may lead to convulsive seizures.

Quinolone-class drugs have been associated with cartilage erosions in weight-bearing joints and other forms of arthropathy in immature animals of various species.

The use of fluoroquinolones in cats has been reported to adversely affect the retina. Such products should be used with caution in cats.

DOSAGE AND ADMINISTRATION:

Enroquin Injectable Solution may be used as the initial dose at 2.5 mg/kg. It should be administered intramuscularly (IM) as a single dose, followed by initiation of enrofloxacin tablet therapy.

Enroquin Injectable Solution may be administered as follows:

Weight of Animal | Enroquin Injectable Solution [The initial Enroquin injectable administration should be followed 12 hours later by initiation of enrofloxacin tablet therapy.] 2.5 mg/kg
9.1 kg (20 lb) | 1.00 mL
27.2 kg (60 lb) | 3.00 mL

The lower limit of the dose range was based on efficacy studies in dogs where enrofloxacin was administered at 2.5 mg/kg twice daily. Target animal safety and toxicology studies were used to establish the upper limit of the dose range and treatment duration.

STORAGE:

Protect from direct sunlight. Do not freeze. Store at 20° to 25°C (68° to 77°F); excursions permitted between 15° and 30°C (59° and 86°F).

Use within 90 days of first puncture and puncture a maximum of 20 times. Any product remaining after 20 punctures or more than 90 days after initial puncture should be discarded.

HOW SUPPLIED:

NDC Number | Enroquin Injectable Solution 22.7 mg/mL Vial Size
17033-324-20 | 20 mL

REFERENCES:

^1Dougherty, T.J. and Saukkonen, J.J. Membrane Permeability Changes Associated with DNA Gyrase Inhibitors in Escherichia coli. Antimicrob. Agents and Chemoth., V. 28, Aug. 1985: 200- 206.

^2Walker, R.D., et al. Pharmacokinetic Evaluation of Enrofloxacin Administered Orally to Healthy Dogs. Am.J. Res., V. 53, No. 12, Dec. 1992: 2315-2319.

Approved by FDA under ANADA # 200-708

Distributed by:
Dechra Veterinary Products
7015 College Boulevard, Suite 525
Overland Park, KS 66211 USA

Made in India
Neutral Code No. PON/DRUGS/08 22 2288

Enroquin® is a registered trademark of Dechra Veterinary Products, LLC.

©2021 Dechra Veterinary Products, LLC.

Rev. June 2025

204001117

PRINCIPAL DISPLAY PANEL - 20 mL Vial Carton

NDC: 17033-324-20

Enroquin®
(enrofloxacin)
Antibacterial Injectable Solution 2.27%

For The Treatment of Susceptible Bacterial Pathogens In Dogs Only

CAUTION: Federal (U.S.A.) law restricts this drug to use by or on the order of a licensed veterinarian.

Federal law prohibits the extralabel use of this drug in food-producing animals.

Approved by FDA under ANADA # 200-708

Net Contents: 20 mL

Dechra